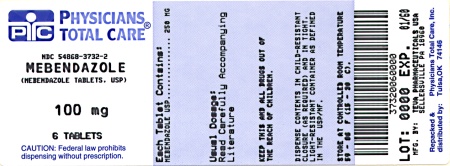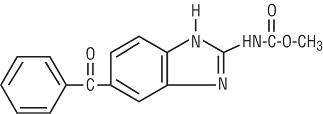 DRUG LABEL: MEBENDAZOLE
NDC: 54868-3732 | Form: TABLET, CHEWABLE
Manufacturer: Physicians Total Care, Inc.
Category: prescription | Type: HUMAN PRESCRIPTION DRUG LABEL
Date: 20100429

ACTIVE INGREDIENTS: MEBENDAZOLE 100 mg/1 1
INACTIVE INGREDIENTS: ANHYDROUS LACTOSE; STARCH, CORN; MAGNESIUM STEARATE; CELLULOSE, MICROCRYSTALLINE; SODIUM LAURYL SULFATE; SACCHARIN SODIUM; SODIUM STARCH GLYCOLATE TYPE A POTATO; STEARIC ACID; FD&C YELLOW NO. 6

MEBENDAZOLE TABLETS, USP 100 mg
9107

DESCRIPTION

Mebendazole is a (synthetic) broad-spectrum anthelmintic available as chewable tablets, each containing 100 mg of mebendazole. Inactive ingredients are: anhydrous lactose NF, corn starch, magnesium stearate, microcrystalline cellulose, sodium lauryl sulfate, sodium saccharin, sodium starch glycolate, stearic acid, and FD&C Yellow #6.

Mebendazole is methyl 5-benzoylbenzimidazole-2-carbamate and has the following structural formula:

Molecular Formula: C16H13N3O3

Mebendazole is a white to slightly yellow powder with a molecular weight of 295.29. It is less than 0.05% soluble in water, dilute mineral acid solutions, alcohol, ether and chloroform, but is soluble in formic acid.

CLINICAL PHARMACOLOGY

Following administration of 100 mg twice daily for three consecutive days, plasma levels of mebendazole and its primary metabolite, the 2-amine, do not exceed 0.03 mcg/mL and 0.09 mcg/mL, respectively. All metabolites are devoid of anthelmintic activity. In man, approximately 2% of administered mebendazole is excreted in urine and the remainder in the feces as unchanged drug or a primary metabolite.

Mode of Action

Mebendazole inhibits the formation of the worms’ microtubules and causes the worms’ glucose depletion.

INDICATIONS AND USAGE

Mebendazole tablets are indicated for the treatment of Enterobius vermicularis (pinworm), Trichuris trichiura (whipworm), Ascaris lumbricoides (common roundworm), Ancylostoma duodenale (common hookworm), Necator americanus (American hookworm) in single or mixed infections.

Efficacy varies as a function of such factors as preexisting diarrhea and gastrointestinal transit time, degree of infection, and helminth strains. Efficacy rates derived from various studies are shown in the table below:

 | Pinworm (enterobiasis) | Whipworm (trichuriasis) | Common Roundworm (ascariasis) | Hookworm
Cure rates mean | 95% | 68% | 98% | 96%
Egg reduction mean | — | 93% | 99% | 99%

CONTRAINDICATIONS

Mebendazole is contraindicated in persons who have shown hypersensitivity to the drug.

WARNINGS

There is no evidence that mebendazole, even at high doses, is effective for hydatid disease. There have been rare reports of neutropenia and agranulocytosis when mebendazole was taken for prolonged periods and at dosages substantially above those recommended.

PRECAUTIONS

General

Periodic assessment of organ system functions, including hematopoietic and hepatic, is advisable during prolonged therapy.

Information for Patients

Patients should be informed of the potential risk to the fetus in women taking mebendazole during pregnancy, especially during the first trimester (See Pregnancy).

Patients should also be informed that cleanliness is important to prevent reinfection and transmission of the infection.

Drug Interactions

Preliminary evidence suggests that cimetidine inhibits mebendazole metabolism and may result in an increase in plasma concentrations of mebendazole.

Carcinogenesis, Mutagenesis, Impairment of Fertility

In carcinogenicity tests of mebendazole in mice and rats, no carcinogenic effects were seen at doses as high as 40 mg/kg (one to two times the human dose, based on mg/m^2) given daily over two years. Dominant lethal mutation tests in mice showed no mutagenicity at single doses as high as 640 mg/kg (18 times the human dose, based on mg/m^2). Neither the spermatocyte test, the F1 translocation test, nor the Ames test indicated mutagenic properties. Doses up to 40 mg/kg in mice (equal to the human dose, based on mg/m^2), given to males for 60 days and to females for 14 days prior to gestation, had no effect upon fetuses and offspring, though there was slight maternal toxicity.

Pregnancy

Teratogenic Effects

Pregnancy category C

Mebendazole has shown embryotoxic and teratogenic activity in pregnant rats at single oral doses as low as 10 mg/kg (approximately equal to the human dose, based on mg/m^2). In view of these findings the use of mebendazole is not recommended in pregnant women. Although there are no adequate and well-controlled studies in pregnant women, a postmarketing survey has been done of a limited number of women who inadvertently had consumed mebendazole during the first trimester of pregnancy. The incidence of spontaneous abortion and malformation did not exceed that in the general population. In 170 deliveries on term, no teratogenic risk of mebendazole was identified.

Nursing Mothers

It is not known whether mebendazole is excreted in human milk. Because many drugs are excreted in human milk, caution should be exercised when mebendazole is administered to a nursing woman.

Pediatric Use

The drug has not been extensively studied in children under two years; therefore, in the treatment of children under two years the relative benefit/risk should be considered.

ADVERSE REACTIONS

Gastrointestinal

Transient symptoms of abdominal pain and diarrhea in cases of massive infection and expulsion of worms.

Hypersensitivity

Rash, urticaria and angioedema have been observed on rare occasions.

Central Nervous System

Very rare cases of convulsions have been reported.

Liver

There have been liver function test elevations [AST (SGOT), ALT (SGPT), and GGT] and rare reports of hepatitis when mebendazole was taken for prolonged periods and at dosages substantially above those recommended.

Hematologic

Neutropenia and agranulocytosis. (See WARNINGS).

OVERDOSAGE

In the event of accidental overdosage, gastrointestinal complaints lasting up to a few hours may occur. Vomiting and purging should be induced.

DOSAGE AND ADMINISTRATION

The same dosage schedule applies to children and adults. The tablet may be chewed, swallowed, or crushed and mixed with food.

 | Pinworm (enterobiasis) | Whipworm (trichuriasis) | Common Roundworm (ascariasis) | Hookworm
Dose | 1 tablet, once | 1 tablet morning and evening for 3 consecutive days | 1 tablet morning and evening for 3 consecutive days | 1 tablet morning and evening for 3 consecutive days

If the patient is not cured three weeks after treatment, a second course of treatment is advised. No special procedures, such as fasting or purging, are required.

HOW SUPPLIED

Mebendazole 100 mg, chewable, round, light peach-colored, unscored tablets, debossed “93” and “107” on one side and plain on the other side, supplied in

Bottles of 2 tablets, blister packaged | NDC 54868-3732-3
Bottles of 6 tablets, blister packaged | NDC 54868-3732-2
Boxes of 12 tablets, blister packaged | NDC 54868-3732-0

Store at 20° to 25°C (68° to 77°F) [See USP Controlled Room Temperature].

MEBENDAZOLE TABLETS, USP

CHEWABLE TABLET

100 mg

Your doctor has prescribed this medicine to treat an infection caused by an intestinal worm. Follow your doctor’s instructions carefully. In addition to your doctor’s treatment, you can help prevent reinfection and infection of other people by understanding a few simple facts about worms.

PINWORM: Pinworms look like tiny white threads and live in the bowel. Usually at night, they travel to the rectal opening and lay eggs on the outside skin. This sometimes causes itching which may be very annoying. That is why restless sleep is a frequent sign of pinworms, especially in children. Scratching will cause pinworm eggs to stick to the fingers. Reinfection will result if the fingers are placed in the mouth.

The eggs, which are too small to see, contaminate whatever they come in contact with: bedclothes, underwear, hands, and food touched by contaminated hands. Even eggs floating in the air can be swallowed and cause infection. Pinworms are highly contagious. Even the cleanest and most careful people can get them.

To help prevent reinfection follow these rules:

- Wash hands and fingernails with soap often during the day, especially before eating and after using the toilet.
- Wear tight underpants both day and night. Change them daily.
- For several days after treatment, clean the bedroom floor by vacuuming or damp mopping. Avoid dry sweeping that may stir up dust.
- After treatment, wash bed linens and night clothes (don’t shake them).
- Keep the toilet seats clean

HOOKWORM, WHIPWORM AND ROUNDWORM: These worms also live in the bowel.

Eggs from the worms are deposited in the soil if an infected person fails to use a toilet or bathroom. Since the eggs can live only in warm soil, they are found most often where the soil never freezes in winter. People living or traveling in areas with warm winters may have these infections. The eggs in the soil are usually carried to the mouth on food or by contact with dirty hands. In the case of hookworms a pre-adult form of the worm actually penetrates the skin (usually the foot) and burrows its way into the bloodstream. Once inside the body, they grow and breed inside the bowel. New eggs are released in the feces.

Therefore, poor sewage disposal or the use of human waste for fertilizer can contaminate the ground with new eggs, which can then reinfect people.

The medication used to treat these worms causes them to be expelled from the body. Hookworms and whipworms may be seen and resemble small white threads. Roundworms are much larger and easily seen.

To help prevent reinfection follow these rules:

- Wash hands and fingernails with soap often during the day, especially before eating and after using the toilet.
- Wash all fruits and vegetables thoroughly or cook them well.
- Wear shoes.
- Use the bathroom.

Follow your doctor’s advice, take the medication he gives you and follow the rules mentioned here. If you have other questions about worms, be sure to ask your doctor.

WARNING: Do not take this medication if you are pregnant or think you may be pregnant. Consult your physician.

Manufactured By:

TEVA PHARMACEUTICALS USA

Sellersville, PA 18960

Rev. D 9/2007

Relabeling and Repackaging by:
Physicians Total Care, Inc.
Tulsa, OK 74146

PRINCIPAL DISPLAY PANEL

100 mg Blister Label Text

MEBENDAZOLE

TABLET USP, 100 mg

Each tablet contains:

Mebendazole, USP 100 mg

USUAL DOSAGE: See package insert for dosage information.

Store at controlled room temperature, between 20° and 25°C (68° and 77°F) (see USP).

KEEP THIS AND ALL MEDICATIONS OUT OF THE REACH OF CHILDREN.

Rx only